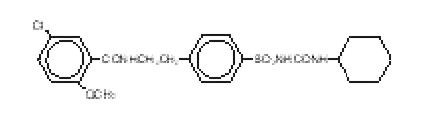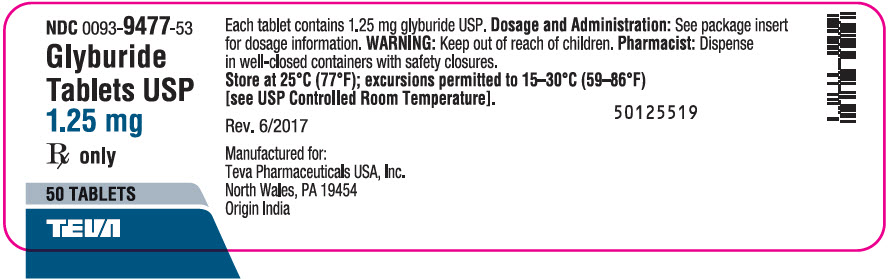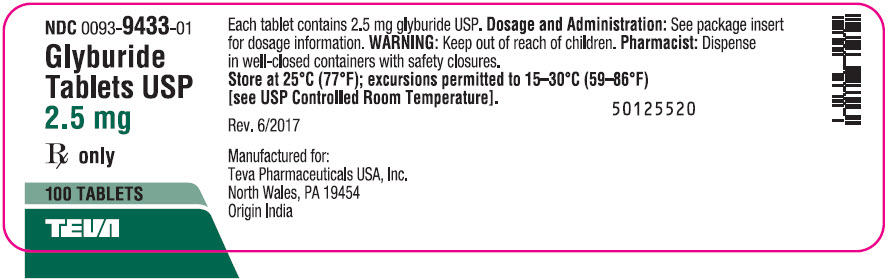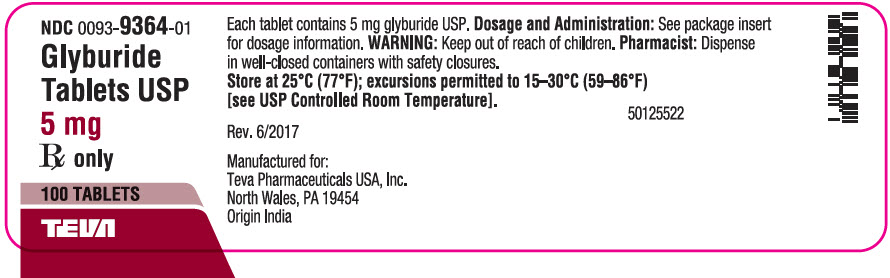 DRUG LABEL: Glyburide
NDC: 0093-9477 | Form: TABLET
Manufacturer: TEVA Pharmaceuticals USA Inc
Category: prescription | Type: HUMAN PRESCRIPTION DRUG LABEL
Date: 20210701

ACTIVE INGREDIENTS: GLYBURIDE 1.25 mg/1 1
INACTIVE INGREDIENTS: ANHYDROUS DIBASIC CALCIUM PHOSPHATE; MAGNESIUM PALMITOSTEARATE; MICROCRYSTALLINE CELLULOSE; SODIUM ALGINATE; TALC

Glyburide Tablets USP

1.25, 2.5 and 5 mg

DESCRIPTION

Glyburide is an oral blood-glucose-lowering drug of the sulfonylurea class. It is a white, crystalline compound, formulated as tablets of 1.25 mg, 2.5 mg, and 5 mg strengths for oral administration. Glyburide tablets USP contain the active ingredient glyburide and the following inactive ingredients: dibasic calcium phosphate USP, magnesium stearate NF, microcrystalline cellulose NF, sodium alginate NF, talc USP. Glyburide 2.5 mg tablets USP also contain FD&C Red #40 Aluminum Lake. Glyburide 5 mg tablets USP also contain FD&C Blue #1 Aluminum Lake. Chemically, Glyburide is identified as 1-[[p-[2-(5-Chloro-o-anisamido)ethyl]phenyl]sulfonyl]-3-cyclohexylurea.

The CAS Registry Number is 10238-21-8.

The structural formula is:

The molecular weight is 493.99. The aqueous solubility of Glyburide increases with pH as a result of salt formation.

CLINICAL PHARMACOLOGY

Glyburide appears to lower the blood glucose acutely by stimulating the release of insulin from the pancreas, an effect dependent upon functioning beta cells in the pancreatic islets. The mechanism by which Glyburide lowers blood glucose during long-term administration has not been clearly established.

With chronic administration in Type II diabetic patients, the blood glucose lowering effect persists despite a gradual decline in the insulin secretory response to the drug. Extrapancreatic effects may play a part in the mechanism of action of oral sulfonylurea hypoglycemic drugs.

In addition to its blood glucose lowering actions, Glyburide produces a mild diuresis by enhancement of renal free water clearance. Clinical experience to date indicates an extremely low incidence of disulfiram-like reactions in patients while taking Glyburide.

Pharmacokinetics

Single-dose studies with Glyburide in normal subjects demonstrate significant absorption within 1 hour, peak drug levels at about 4 hours, and low but detectable levels at 24 hours. Mean serum levels of glyburide, as reflected by areas under the serum concentration-time curve, increase in proportion to corresponding increases in dose. Multiple-dose studies with Glyburide in diabetic patients demonstrate drug level concentration-time curves similar to single-dose studies, indicating no build-up of drug in tissue depots. The decrease of glyburide in the serum of normal healthy individuals is biphasic, the terminal half-life being about 10 hours. In single-dose studies in fasting normal subjects, the degree and duration of blood glucose lowering is proportional to the dose administered and to the area under the drug level concentration-time curve. The blood glucose lowering effect persists for 24 hours following single morning doses in non-fasting diabetic patients. Under conditions of repeated administration in diabetic patients, however, there is no reliable correlation between blood drug levels and fasting blood glucose levels. A one-year study of diabetic patients treated with Glyburide showed no reliable correlation between administered dose and serum drug level.

The major metabolite of Glyburide is the 4-trans-hydroxy derivative. A second metabolite, the 3-cis-hydroxy derivative, also occurs. These metabolites contribute no significant hypoglycemic action since they are only weakly active (1/400th and 1/40th, respectively, as glyburide) in rabbits.

Glyburide is excreted as metabolites in the bile and urine, approximately 50% by each route. This dual excretory pathway is qualitatively different from that of other sulfonylureas, which are excreted primarily in the urine.

Sulfonylurea drugs are extensively bound to serum proteins. Displacement from protein binding sites by other drugs may lead to enhanced hypoglycemic action. In vitro, the protein binding exhibited by Glyburide is predominantly non-ionic, whereas that of other sulfonylureas (chlorpropamide, tolbutamide, tolazamide) is predominantly ionic. Acidic drugs such as phenylbutazone, warfarin, and salicylates displace the ionic-binding sulfonylureas from serum proteins to a far greater extent than the non-ionic binding Glyburide. It has not been shown that this difference in protein binding will result in fewer drug-drug interactions with Glyburide in clinical use.

INDICATIONS AND USAGE

Glyburide is indicated as an adjunct to diet and exercise to improve glycemic control in adults with type 2 diabetes mellitus.

CONTRAINDICATIONS

Glyburide is contraindicated in patients:

1. With known hypersensitivity to the drug or any of its excipients.
2. With type 1 diabetes mellitus or diabetic ketoacidosis, with or without coma.
  These conditions should be treated with insulin.
3. Treated with bosentan.

WARNINGS

SPECIAL WARNING ON INCREASED RISK OF CARDIOVASCULAR MORTALITY

The administration of oral hypoglycemic drugs has been reported to be associated with increased cardiovascular mortality as compared to treatment with diet alone or diet plus insulin. This warning is based on the study conducted by the University Group Diabetes Program (UGDP), a long-term prospective clinical trial designed to evaluate the effectiveness of glucose-lowering drugs in preventing or delaying vascular complications in patients with non-insulin-dependent diabetes. The study involved 823 patients who were randomly assigned to one of four treatment groups (Diabetes 19 (supp. 2): 747–830, 1970).

UGDP reported that patients treated for 5 to 8 years with diet plus a fixed dose of tolbutamide (1.5 grams per day) had a rate of cardiovascular mortality approximately 2-1/2 times that of patients treated with diet alone. A significant increase in total mortality was not observed, but the use of tolbutamide was discontinued based on the increase in cardiovascular mortality, thus limiting the opportunity for the study to show an increase in overall mortality. Despite controversy regarding the interpretation of these results, the findings of the UGDP study provide an adequate basis for this warning. The patient should be informed of the potential risks and advantages of Glyburide and of alternative modes of therapy.

Although only one drug in the sulfonylurea class (tolbutamide) was included in this study, it is prudent from a safety standpoint to consider that this warning may also apply to other oral hypoglycemic drugs in this class, in view of their close similarities in mode of action and chemical structure.

Persons allergic to other sulfonamide derivatives may develop an allergic reaction to glyburide as well.

PRECAUTIONS

General

Macrovascular Outcomes

There have been no clinical studies establishing conclusive evidence of macrovascular risk reduction with Glyburide or any other anti-diabetic drug.

Hypoglycemia

All sulfonylurea drugs are capable of producing severe hypoglycemia. Proper patient selection, dosage, and instructions are important to avoid hypoglycemic episodes. Severe renal or hepatic insufficiency may cause elevated blood levels of Glyburide and the latter may also diminish gluconeogenic capacity, both of which increase the risk of serious, prolonged hypoglycemic reactions. Elderly, debilitated or malnourished patients, and those with adrenal or pituitary insufficiency are particularly susceptible to the hypoglycemic action of glucose-lowering drugs. Hypoglycemia may be difficult to recognize in patients with autonomic neuropathy, the elderly, and in people who are taking beta-adrenergic blocking drugs or other sympatholytic agents.

Hypoglycemia is more likely to occur when caloric intake is deficient, after severe or prolonged exercise, when alcohol is ingested, or when more than one glucose-lowering drug is used. Loss of control of blood glucose: When a patient stabilized on any diabetic regimen is exposed to stress such as fever, trauma, infection, or surgery, a loss of control may occur. At such times, it may be necessary to discontinue Glyburide and administer insulin.

The effectiveness of any oral hypoglycemic drug, including Glyburide, in lowering blood glucose to a desired level decreases in many patients over a period of time, which may be due to progression of the severity of the diabetes or to diminished responsiveness to the drug. This phenomenon is known as secondary failure, to distinguish it from primary failure in which the drug is ineffective in an individual patient when first given.

Hemolytic Anemia

Treatment of patients with glucose 6-phosphate dehydrogenase (G6PD) deficiency with sulfonylurea agents can lead to hemolytic anemia. Because Glyburide belongs to the class of sulfonylurea agents, caution should be used in patients with G6PD deficiency and a non-sulfonylurea alternative should be considered. In postmarketing reports, hemolytic anemia has also been reported in patients who did not have known G6PD deficiency.

Information for Patients

Patients should be informed of the potential risks and advantages of Glyburide and of alternative modes of therapy. They should also be informed about the importance of adherence to dietary instructions, of a regular exercise program, and of regular testing of blood glucose.

The risks of hypoglycemia, its symptoms and treatment, and conditions that predispose to its development should be explained to patients and responsible family members. Primary and secondary failure should also be explained.

Laboratory Tests

Periodic fasting blood glucose measurements should be performed to monitor therapeutic response. A glycosylated hemoglobin determination should also be performed periodically.

Drug Interactions

The hypoglycemic action of sulfonylureas may be potentiated by certain drugs including nonsteroidal anti-inflammatory agents, ACE inhibitors, disopyramide, fluoxetine, clarithromycin, and other drugs that are highly protein bound, salicylates, sulfonamides, chloramphenicol, probenecid, monoamine oxidase inhibitors, and beta adrenergic blocking agents. When such drugs are administered to a patient receiving Glyburide, the patient should be observed closely for hypoglycemia. When such drugs are withdrawn from a patient receiving Glyburide, the patient should be observed closely for loss of control.

An increased incidence of elevated liver enzymes was observed in patients receiving glyburide concomitantly with bosentan. Therefore concomitant administration of glyburide and bosentan is contraindicated (see CONTRAINDICATIONS).

A potential interaction between oral miconazole and oral hypoglycemic agents leading to severe hypoglycemia has been reported. Whether this interaction also occurs with the intravenous, topical or vaginal preparations of miconazole is not known.

A possible interaction between glyburide and fluoroquinolone antibiotics has been reported resulting in a potentiation of the hypoglycemic action of glyburide. The mechanism for this interaction is not known.

Possible interactions between glyburide and coumarin derivatives have been reported that may either potentiate or weaken the effects of coumarin derivatives. The mechanism of these interactions is not known.

Rifampin may worsen glucose control of glyburide because rifampin can significantly induce metabolic isozymes of glyburide such as CYP2C9 and 3A4.

Certain drugs tend to produce hyperglycemia and may lead to loss of control. These drugs include the thiazides and other diuretics, corticosteroids, phenothiazines, thyroid products, estrogens, oral contraceptives, phenytoin, nicotinic acid, sympathomimetics, calcium channel blocking drugs, and isoniazid. When such drugs are administered to a patient receiving Glyburide, the patient should be closely observed for loss of control. When such drugs are withdrawn from a patient receiving Glyburide, the patient should be observed closely for hypoglycemia.

Glyburide may increase cyclosporine plasma concentration and potentially lead to its increased toxicity. Monitoring and dosage adjustment of cyclosporine are therefore recommended when both drugs are coadministered.

Colesevelam

Concomitant administration of colesevelam and glyburide resulted in reductions in glyburide AUC and Cmax of 32% and 47%, respectively. When glyburide was administered 1 hour before colesevelam, the reductions in glyburide AUC and Cmax were 20% and 15%, respectively, and not significantly changed (-7% and 4%, respectively) when administered 4 hours before colesevelam. Therefore, glyburide should be administered at least 4 hours prior to colesevelam.

Glyburide is mainly metabolized by CYP 2C9 and to a lesser extent by CYP 3A4. There is a potential for drug-drug interaction when glyburide is coadministered with inducers or inhibitors of CYP 2C9, which should be taken into account when considering concomitant therapy.

Carcinogenesis, Mutagenesis, and Impairment of Fertility

Glyburide is non-mutagenic when studied in the Salmonella microsome test (Ames test) and in the DNA damage/alkaline elution assay. Studies in rats at doses up to 300 mg/kg/day for 18 months showed no carcinogenic effects.

No drug related effects were noted in any of the criteria evaluated in the two year oncogenicity study of glyburide in mice.

Pregnancy

Teratogenic Effects

Glyburide has been shown to affect the maturation of the long bones (humerus and femur) in rat pups when given in doses 6250 times the maximum recommended human dose. These effects, which were seen during the period of lactation and not during organogenesis, are a shortening of the bones with effects to various structures of the long bones, especially in humerus and femur.

There are no adequate and well-controlled studies in pregnant women. Because animal reproduction studies are not always predictive of human response, Glyburide should be used during pregnancy only if the potential benefit justifies the risk to the fetus. Because recent information suggests that abnormal blood glucose levels during pregnancy are associated with a higher incidence of congenital abnormalities, many experts recommend that insulin be used during pregnancy to maintain blood glucose levels as close to normal as possible.

Nonteratogenic Effects

Prolonged severe hypoglycemia (4 to 10 days) has been reported in neonates born to mothers who were receiving a sulfonylurea drug at the time of delivery. This has been reported more frequently with the use of agents with prolonged half-lives. If Glyburide is used during pregnancy, it should be discontinued at least two weeks before the expected delivery date.

Nursing Mothers

Although it is not known whether Glyburide is excreted in human milk, some sulfonylureas are known to be excreted in human milk. Because the potential for hypoglycemia in nursing infants may exist, a decision should be made whether to discontinue nursing or to discontinue administering the drug, taking into account the importance of the drug to the mother. If Glyburide is discontinued and if diet alone is inadequate for controlling blood glucose, insulin therapy should be considered.

Pediatric Use

Safety and effectiveness in pediatric patients have not been established.

Geriatric Use

In US clinical studies of glyburide, 1406 of 2897 patients were ≥60 years and 515 patients were ≥70 years. Differences in safety and efficacy were not determined between these patients and younger patients, but greater sensitivity of some older individuals cannot be ruled out.

Elderly patients are particularly susceptible to hypoglycemic action of glucose-lowering drugs. Hypoglycemia may be difficult to recognize in the elderly (see PRECAUTIONS). The initial and maintenance dosing should be conservative to avoid hypoglycemic reactions.

In three published studies of 20 to 51 subjects each, mixed results were seen in comparing the pharmacokinetics of glyburide in elderly versus younger subjects. However, observed pharmacodynamic differences indicate the necessity for dosage titration to a specified therapeutic response.

This drug is known to be substantially excreted by the kidney, and the risk of toxic reactions to this drug may be greater in patients with impaired renal function. Because elderly patients are more likely to have decreased renal function, care should be taken in dose selection, and it may be useful to monitor renal function.

In elderly, debilitated, or malnourished patients, or in patients with renal or hepatic insufficiency, the initial dosing, dose increments, and maintenance dosage should be conservative to avoid hypoglycemic reactions. Hypoglycemia may be difficult to recognize in the elderly and in people who are taking beta-adrenergic blocking drugs or other sympatholytic agents. (See PRECAUTIONS, General; and DOSAGE AND ADMINISTRATION.)

ADVERSE REACTIONS

Hypoglycemia

See PRECAUTIONS and OVERDOSAGE Sections.

Gastrointestinal Reactions

Cholestatic jaundice and hepatitis may occur rarely which may progress to liver failure; Glyburide should be discontinued if this occurs. Liver function abnormalities, including isolated transaminase elevations, have been reported. Gastrointestinal disturbances, e.g., nausea, epigastric fullness, and heartburn, are the most common reactions and occur in 1.8% of treated patients. They tend to be dose-related and may disappear when dosage is reduced.

Dermatologic Reactions

Allergic skin reactions, e.g., pruritus, erythema, urticaria, and morbilliform or maculopapular eruptions, occur in 1.5% of treated patients. These may be transient and may disappear despite continued use of Glyburide. Bullous reactions, erythema multiforme, and exfoliative dermatitis, have been reported. If skin reactions persist, the drug should be discontinued.

Porphyria cutanea tarda and photosensitivity reactions have been reported with sulfonylureas.

Hematologic Reactions

Leukopenia, agranulocytosis, thrombocytopenia, which occasionally may present as purpura, hemolytic anemia, aplastic anemia, and pancytopenia have been reported with sulfonylureas.

Metabolic Reactions

Hepatic porphyria reactions have been reported with sulfonylureas; however, these have not been reported with Glyburide. Disulfiram-like reactions have been reported very rarely with Glyburide. Cases of hyponatremia have been reported with glyburide and all other sulfonylureas, most often in patients who are on other medications or have medical conditions known to cause hyponatremia or increase release of antidiuretic hormone. The syndrome of inappropriate antidiuretic hormone (SIADH) secretion has been reported with certain other sulfonylureas, and it has been suggested that these sulfonylureas may augment the peripheral (antidiuretic) action of ADH and/or increase release of ADH. Glyburide can cause weight gain.

Other Reactions

Changes in accommodation and/or blurred vision have been reported with glyburide and other sulfonylureas. These are thought to be related to fluctuation in glucose levels.

In addition to dermatologic reactions, allergic reactions such as angioedema, arthralgia, myalgia and vasculitis have been reported.

OVERDOSAGE

Overdosage of sulfonylureas, including Glyburide, can produce hypoglycemia. Mild hypoglycemic symptoms without loss of consciousness or neurologic findings should be treated aggressively with oral glucose and adjustments in drug dosage and/or meal patterns. Close monitoring should continue until the physician is assured that the patient is out of danger. Severe hypoglycemic reactions with coma, seizure, or other neurological impairment occur infrequently, but constitute medical emergencies requiring immediate hospitalization. If hypoglycemic coma is diagnosed or suspected, the patient should be given a rapid intravenous injection of concentrated (50%) glucose solution. This should be followed by a continuous infusion of a more dilute (10%) glucose solution at a rate that will maintain the blood glucose at a level above 100 mg/dL. Patients should be closely monitored for a minimum of 24 to 48 hours, since hypoglycemia may recur after apparent clinical recovery.

DOSAGE AND ADMINISTRATION

There is no fixed dosage regimen for the management of diabetes mellitus with Glyburide or any other hypoglycemic agent. The patient's fasting blood glucose must be measured periodically to determine the minimum effective dose for the patient; to detect primary failure, i.e., inadequate lowering of blood glucose at the maximum recommended dose of medication; and to detect secondary failure, i.e., loss of adequate blood glucose lowering response after an initial period of effectiveness. Periodic glycosylated hemoglobin determinations should be performed.

Short-term administration of Glyburide may be sufficient during periods of transient loss of control in patients usually controlled well on diet.

1. Usual Starting Dose

The usual starting dose of Glyburide as initial therapy is 2.5 to 5 mg daily, administered with breakfast or the first main meal. Those patients who may be more sensitive to hypoglycemic drugs should be started at 1.25 mg daily. (See PRECAUTIONS Section for patients at increased risk). Failure to follow an appropriate dosage regimen may precipitate hypoglycemia. Patients who do not adhere to their prescribed dietary and drug regimen are more prone to exhibit unsatisfactory response to therapy.

Transfer of patients from other oral antidiabetic regimens to Glyburide should be done conservatively and the initial daily dose should be 2.5 to 5 mg. When transferring patients from oral hypoglycemic agents other than chlorpropamide, to Glyburide, no transition period and no initial priming dose is necessary. When transferring patients from chlorpropamide, particular care should be exercised during the first two weeks because the prolonged retention of chlorpropamide in the body and subsequent overlapping drug effects may provoke hypoglycemia.

Bioavailability studies have demonstrated that Glynase® [Trademarks of their respective owners, not affiliated with sanofi-aventis.] PresTab® Tablets 3 mg are not bioequivalent to Glyburide tablets USP 5 mg. Therefore, these products are not substitutable and patients should be retitrated if transferred.

Some Type II diabetic patients being treated with insulin may respond satisfactorily to Glyburide. If the insulin dose is less than 20 units daily, substitution of Glyburide 2.5 to 5 mg as a single daily dose may be tried. If the insulin dose is between 20 and 40 units daily, the patient may be placed directly on Glyburide 5 mg daily as a single dose. If the insulin dose is more than 40 units daily, a transition period is required for conversion to Glyburide. In these patients, insulin dosage is decreased by 50% and Glyburide 5 mg daily is started. Please refer to Usual Maintenance Dose for further explanation.

When colesevelam is coadministered with glyburide, maximum plasma concentration and total exposure to glyburide is reduced. Therefore, glyburide should be administered at least 4 hours prior to colesevelam.

2. Usual Maintenance Dose

The usual maintenance dose is in the range of 1.25 to 20 mg daily, which may be given as a single dose or in divided doses (See Dosage Interval Section). Dosage increases should be made in increments of no more than 2.5 mg at weekly intervals based upon the patient's blood glucose response.

No exact dosage relationship exists between Glyburide and the other oral hypoglycemic agents. Although patients may be transferred from the maximum dose of other sulfonylureas, the maximum starting dose of 5 mg of Glyburide should be observed. A maintenance dose of 5 mg Glyburide provides approximately the same degree of blood glucose control as 250 to 375 mg chlorpropamide, 250 to 375 mg tolazamide, 500 to 750 mg acetohexamide, or 1000 to 1500 mg tolbutamide.

When transferring patients receiving more than 40 units of insulin daily, they may be started on a daily dose of Glyburide 5 mg concomitantly with a 50% reduction in insulin dose. Progressive withdrawal of insulin and increase of Glyburide in increments of 1.25 to 2.5 mg every 2 to 10 days is then carried out. During this conversion period when both insulin and Glyburide are being used, hypoglycemia may rarely occur. During insulin withdrawal, patients should self-test their blood for glucose and their urine for acetone at least 3 times daily and report results to their physician. Self-testing of urinary glucose is a less desirable alternative. The appearance of persistent acetonuria with glycosuria indicates that the patient is a Type I diabetic who requires insulin therapy.

3. Maximum Dose

Daily doses of more than 20 mg are not recommended.

4. Dosage Interval

Once-a-day therapy is usually satisfactory, based upon usual meal patterns and a 10 hour half-life of Glyburide. Some patients, particularly those receiving more than 10 mg daily, may have a more satisfactory response with twice-a-day dosage.

In elderly patients, debilitated or malnourished patients, and patients with impaired renal or hepatic function, the initial and maintenance dosing should be conservative to avoid hypoglycemic reactions. (See PRECAUTIONS Section.)

HOW SUPPLIED

Glyburide tablets USP are available in the following strengths and package sizes:

1.25 mg (white to off-white, capsule-shaped, flat faced, beveled edge tablet debossed "GLYBUR" on one side and a score line on the other side).
Bottles of 50 (NDC 0093-9477-53)

2.5 mg (pink, capsule-shaped, flat faced, beveled edge tablet debossed "GLYBUR" on one side and a score line on the other side).
Bottles of 100 (NDC 0093-9433-01)
Bottles of 500 (NDC 0093-9433-05)

5 mg (blue, capsule-shaped, flat faced, beveled edge tablet debossed "GLYBUR" on one side and a score line on the other side).
Bottles of 100 (NDC 0093-9364-01)
Bottles of 500 (NDC 0093-9364-05)
Bottles of 1000 (NDC 0093-9364-10)

STORAGE AND HANDLING

Store at 25°C (77°F); excursions permitted to 15–30°C (59–86°F) [See USP Controlled Room Temperature].

Dispense in well-closed containers with safety closures.

Revised April 2018

Manufactured for:
Teva Pharmaceuticals USA, Inc.
North Wales, PA 19454

©2018 sanofi-aventis U.S. LLC

PRINCIPAL DISPLAY PANEL - 1.25 mg Tablet Bottle Label

NDC 0093-9477-53

Glyburide
Tablets USP
1.25 mg

Rx only

50 TABLETS

TEVA

PRINCIPAL DISPLAY PANEL - 2.5 mg Tablet Bottle Label

NDC 0093-9433-01

Glyburide
Tablets USP
2.5 mg

Rx only

100 TABLETS

TEVA

PRINCIPAL DISPLAY PANEL - 5 mg Tablet Bottle Label

NDC 0093-9364-01

Glyburide
Tablets USP
5 mg

Rx only

100 TABLETS

TEVA